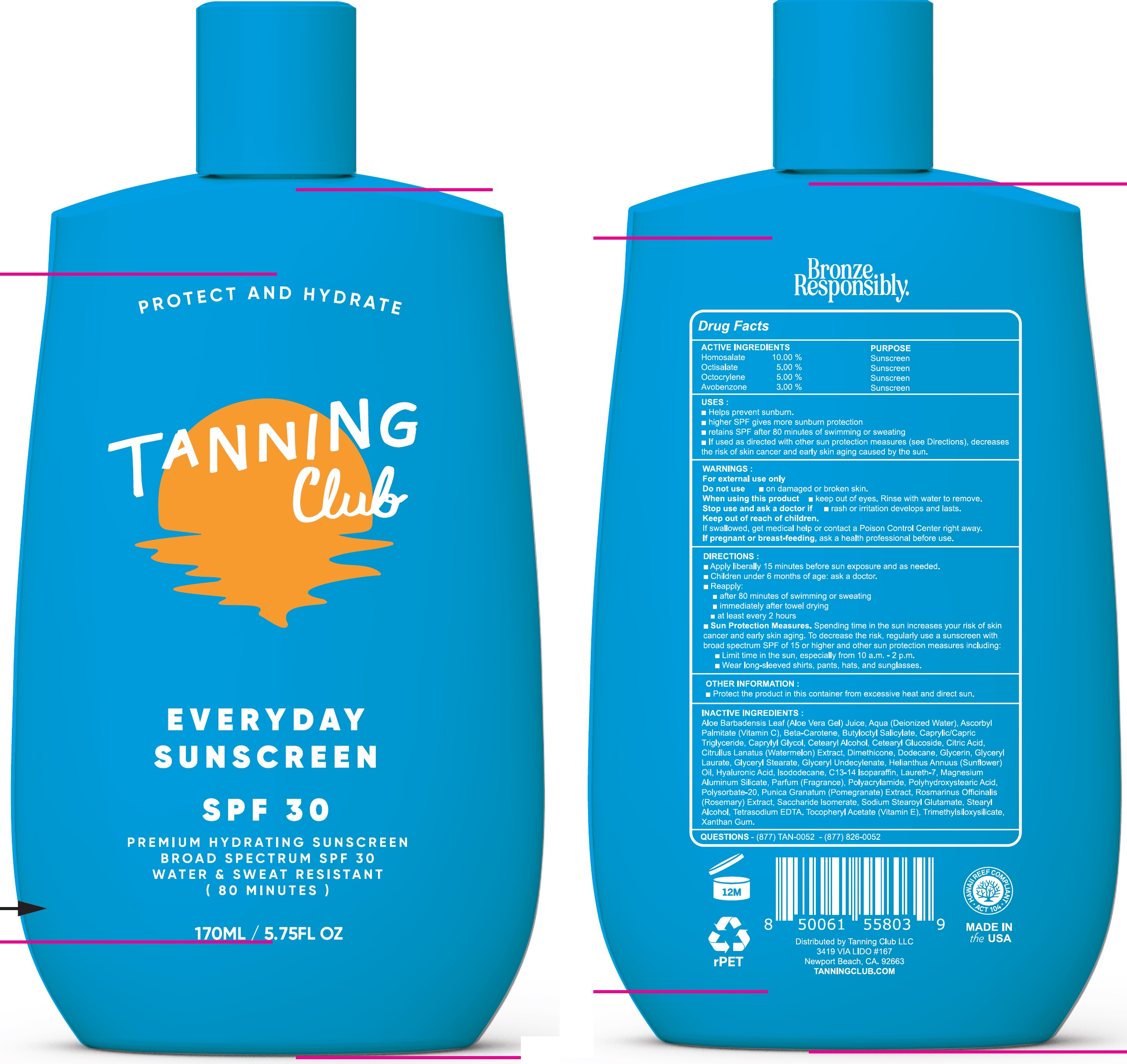 DRUG LABEL: Tanning Club Everyday Sunscreen SPF 30
NDC: 84562-871 | Form: LOTION
Manufacturer: TANNING CLUB, LLC
Category: otc | Type: HUMAN OTC DRUG LABEL
Date: 20250806

ACTIVE INGREDIENTS: HOMOSALATE 100 mg/1 mL; OCTISALATE 50 mg/1 mL; OCTOCRYLENE 50 mg/1 mL; AVOBENZONE 30 mg/1 mL
INACTIVE INGREDIENTS: ALOE VERA LEAF JUICE; WATER; ASCORBYL PALMITATE; BETA-CAROTENE; BUTYLOCTYL SALICYLATE; MEDIUM-CHAIN TRIGLYCERIDES; CAPRYLYL GLYCOL; CETEARYL ALCOHOL; CETEARYL GLUCOSIDE; CITRIC ACID MONOHYDRATE; WATERMELON; DIMETHICONE; DODECANE; GLYCERIN; GLYCERYL LAURATE; GLYCERYL MONOSTEARATE; HELIANTHUS ANNUUS FLOWERING TOP; HYALURONIC ACID; ISODODECANE; C13-14 ISOPARAFFIN; LAURETH-7; MAGNESIUM ALUMINUM SILICATE; POLYSORBATE 20; POMEGRANATE; ROSEMARY; SACCHARIDE ISOMERATE; SODIUM STEAROYL GLUTAMATE; STEARYL ALCOHOL; EDETATE SODIUM; .ALPHA.-TOCOPHEROL ACETATE; XANTHAN GUM

Tanning Club Everyday Sunscreen SPF 30

ACTIVE INGREDIENTS

Homosalate 10.00%
Octisalate 5.00%
Octocrylene 5.00%
Avobenzone 3.00%

PURPOSE

Sunscreen

USES:

- Helps prevent sunburn.
- higher SPF gives more sunburn protection
- retains SPF after 80 minutes of swimming or sweating
- If used as directed with other sun protection measures (see Directions), decreases the risk of skin cancer and early skin aging caused by the sun.

WARNINGS:

For external use only

Do not use

- on damaged or broken skin.

When using this product

- keep out of eyes. Rinse with water to remove.

Stop use and ask a doctor if

- rash or irritation develops and lasts.

Keep out of reach of children.

If swallowed, get medical help or contact a Poison Control Center right away.

If pregnant or breast-feeding,

ask a health professional before use.

DIRECTIONS:

- Apply liberally 15 minutes before sun exposure and as needed.
- Children under 6 months of age: ask a doctor.
- Reapply:
- after 80 minutes of swimming or sweating
- immediately after towel drying
- at least every 2 hours
- Sun Protection Measures.Spending time in the sun increases your risk of skin cancer and early skin aging. To decrease the risk, regularly use a sunscreen with broad spectrum SPF of 15 or higher and other sun protection measures including:
- Limit time in the sun, especially from 10 a.m.-2 p.m.
- Wear long-sleeved shirts, pants, hats, and sunglasses.

OTHER INFORMATION:

- Protect the product in this container from excessive heat and direct sun.

INACTIVE INGREDIENTS:

Aloe Barbadensis Leaf (Aloe Vera Gel) Juice, Aqua (Deionized Water), Ascorbyl Palmitate (Vitamine C), Beta-Carotene, Butyloctyl Salicylate, Caprylic/Capric Triglyceride, Caprylyl Glycol, Cetearyl Alcohol, Cetearyl Glucoside, Citric Acid, Citrullus Lanatus (Watermelon) Extract, Dimethicone, Dodecane, Glycerin, Glyceryl Laurate, Glyceryl Stearate, Glyceryl Undecylenate, Helianthus Annuus (Sunflower) Oil, Hyaluronic Acid, Isododecane, C13-14 Isoparaffin, Laureth-7, Magnesium aluminum Silicate, Parfum (Fragrance), Polyacrylamide, Polyhydroxystearic Acid, Polysorbate-20, Punica Granatum (Pomegranate) Extract, Rosmarinus Officinalis (Rosemary) Extract, Saccharide Isomerate, Sodium Stearoyl Glutamate, Stearyl Alcohol, Tetrasodium EDTA, Tocopheryl Acetate (Vitamin E), Trimethylsiloxysilicate, Xanthan Gum.

QUESTIONS

- (877) TAN-0052 - (877) 826-0052